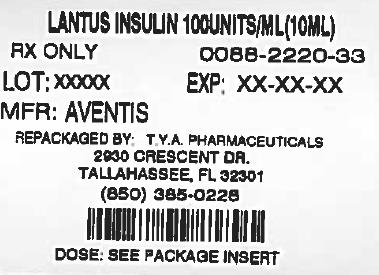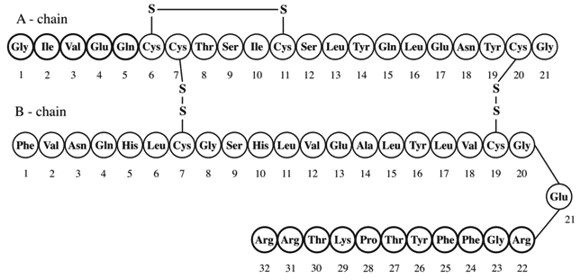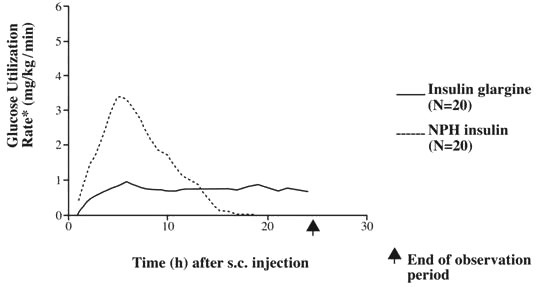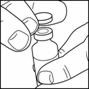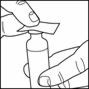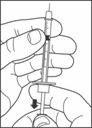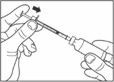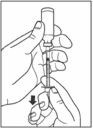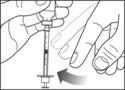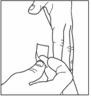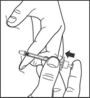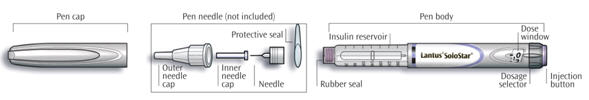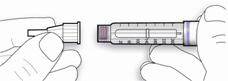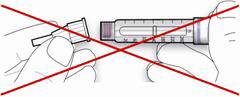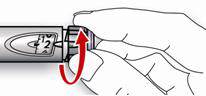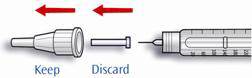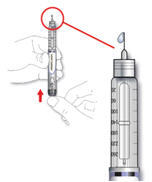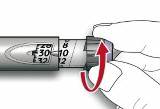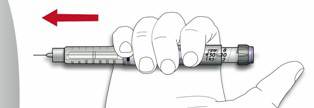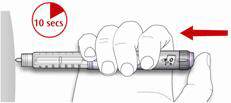 DRUG LABEL: Lantus
NDC: 64725-2220 | Form: INJECTION, SOLUTION
Manufacturer: TYA Pharmaceuticals
Category: prescription | Type: HUMAN PRESCRIPTION DRUG LABEL
Date: 20140109

ACTIVE INGREDIENTS: insulin glargine 100 [iU]/1 mL
INACTIVE INGREDIENTS: ZINC 30 ug/1 mL; METACRESOL 2.7 mg/1 mL; GLYCERIN 20 mg/1 mL; WATER; HYDROCHLORIC ACID; SODIUM HYDROXIDE

HIGHLIGHTS OF PRESCRIBING INFORMATION

These highlights do not include all the information needed to use LANTUS safely and effectively. See full prescribing information for LANTUS. LANTUS (insulin glargine [rDNA origin] injection) solution for subcutaneous injection Initial U.S. Approval: 2000

RECENT MAJOR CHANGES

Warnings and Precautions () 5.8 | 10/2013

1. INDICATIONS AND USAGE

LANTUS is a long- acting human insulin analog indicated to improve glycemic control in adults and pediatric patients with type 1 diabetes mellitus and in adults with type 2 diabetes mellitus. () 1

Important Limitations of Use:

- Not recommended for treating diabetic ketoacidosis. Use intravenous, short-acting insulin instead.

2. DOSAGE AND ADMINISTRATION

- Individualize dose based on the type of diabetes and whether the patient is insulin-naïve (, ,) 2.12.22.3
- Administer subcutaneously once daily at any time of day, but at the same time every day. () 2.1
- Rotate injection sites within an injection area (abdomen, thigh, or deltoid) to reduce the risk of lipodystrophy. () 2.1
- Converting from other insulin therapies may require adjustment of timing and dose of LANTUS. Closely monitor glucoses especially upon converting to LANTUS and during the initial weeks thereafter. () 2.3

3. DOSAGE FORMS AND STRENGTHS

Solution for injection 100 units/mL (U-100) in

- 10 mL vials
- 3 mL SoloStar disposable insulin device () 3

4. CONTRAINDICATIONS

In patients with hypersensitivity to LANTUS or one of its excipients () 4

5. WARNINGS AND PRECAUTIONS

- Dose adjustment and monitoring: Monitor blood glucose in all patients treated with insulin. Modify insulin regimen cautiously and only under medical supervision () 5.1
- Administration: Do not dilute or mix with any other insulin or solution. Do not administer subcutaneously via an insulin pump or intravenously because severe hypoglycemia can occur () 5.2
- Do not share reusable or disposable insulin devices or needles between patients () 5.2
- Hypoglycemia: May be life-threatening. Monitor glucose, administer rescue therapy and treat underlying cause.(,) 5.36.1
- Allergic reactions: Severe, life-threatening, generalized allergy, including anaphylaxis, can occur. Discontinue LANTUS. monitor and treat if indicated (,) 5.46.1
- Renal or hepatic impairment: Reduce dose of LANTUS if indicated (,) 5.55.6
- : Observe for signs and symptoms of heart failure; consider dosage reduction or discontinuation of TZD if heart failure occurs () Fluid retention and heart failure can occur with concomitant use of thiazolidinediones (TZDs)5.8

6. ADVERSE REACTIONS

Adverse reactions commonly associated with LANTUS include hypoglycemia, allergic reactions, injection site reactions, lipodystrophy, pruritus, rash, edema and weight gain. () 6.1

To report SUSPECTED ADVERSE REACTIONS, contact sanofi-aventis at 1-800-633-1610 or FDA at 1-800-FDA-1088 or www.fda.gov/medwatch.

7. DRUG INTERACTIONS

- Certain drugs may affect glucose metabolism, requiring insulin dose adjustment and close monitoring of blood glucose. () 7
- The signs of hypoglycemia may be reduced or absent in patients taking anti-adrenergic drugs (e.g., beta-blockers, clonidine, guanethidine, and reserpine). () 7

8. USE IN SPECIFIC POPULATIONS

- Pregnancy category C: Use during pregnancy only if the potential benefit justifies the potential risk to the fetus () 8.1
- Pediatric: Has not been studied in children with type 2 diabetes. Has not been studied in children with type 1 diabetes <6 years of age () 8.4

FULL PRESCRIBING INFORMATION

1. INDICATIONS AND USAGE

LANTUS is indicated to improve glycemic control in adults and pediatric patients with type 1 diabetes mellitus and in adults with type 2 diabetes mellitus.

Important Limitations of Use:

- LANTUS is not recommended for the treatment of diabetic ketoacidosis. Intravenous short-acting insulin is the preferred treatment for this condition.

2. DOSAGE AND ADMINISTRATION

2.1 Dosing

LANTUS is a recombinant human insulin analog for once daily subcutaneous administration with potency that is approximately the same as the potency of human insulin. LANTUS exhibits a relatively constant glucose-lowering profile over 24 hours that permits once-daily dosing.

LANTUS may be administered at any time during the day. LANTUS should be administered subcutaneously once a day at the same time every day. The dose of LANTUS must be individualized based on clinical response. Blood glucose monitoring is essential in all patients receiving insulin therapy.

Patients adjusting the amount or timing of dosing with LANTUS, should only do so under medical supervision with appropriate glucose monitoring .] [see Warnings and Precautions (5.1)

In patients with type 1 diabetes, LANTUS must be used in regimens with short-acting insulin.

The intended duration of activity of LANTUS is dependent on injection into subcutaneous tissue . LANTUS should not be administered intravenously or via an insulin pump. Intravenous administration of the usual subcutaneous dose could result in severe hypoglycemia . [see ] Clinical pharmacology (12.2) [see ] Warnings and Precautions (5.3)

As with all insulins, injection sites should be rotated within the same region (abdomen, thigh, or deltoid) from one injection to the next to reduce the risk of lipodystrophy [See ]. Adverse Reactions (6.1)

In clinical studies, there was no clinically relevant difference in insulin glargine absorption after abdominal, deltoid, or thigh subcutaneous administration. As for all insulins, the rate of absorption, and consequently the onset and duration of action, may be affected by exercise and other variables, such as stress, intercurrent illness, or changes in co-administered drugs or meal patterns .

2.2 Initiation of LANTUS therapy

The recommended starting dose of LANTUS in patients with type 1 diabetes should be approximately one-third of the total daily insulin requirements. Short-acting, premeal insulin should be used to satisfy the remainder of the daily insulin requirements.

The recommended starting dose of LANTUS in patients with type 2 diabetes who are not currently treated with insulin is 10 units (or 0.2 Units/kg) once daily, which should subsequently be adjusted to the patient's needs.

The dose of LANTUS should be adjusted according to blood glucose measurements. The dosage of LANTUS should be individualized under the supervision of a healthcare provider in accordance with the needs of the patient.

2.3 Converting to LANTUS from other insulin therapies

If changing from a treatment regimen with an intermediate-or long-acting insulin to a regimen with LANTUS, the amount and timing of shorter-acting insulins and doses of any oral anti-diabetic drugs may need to be adjusted.

- If transferring patients from once-daily NPH insulin to once-daily LANTUS, the recommended initial LANTUS dose is the same as the dose of NPH that is being discontinued.
- If transferring patients from twice-daily NPH insulin to once-daily LANTUS, the recommended initial LANTUS dose is 80% of the total NPH dose that is being discontinued. This dose reduction will lower the likelihood of hypoglycemia [ see ]. Warnings and Precautions (5.3)

3. DOSAGE FORMS AND STRENGTHS

LANTUS solution for injection 100 Units per mL is available as:

- 10 mL Vial (1000 Units/10 mL)
- 3 mL SoloStar disposable insulin device (300 Units/3 mL) ®

4. CONTRAINDICATIONS

LANTUS is contraindicated

- In patients with hypersensitivity to LANTUS or one of its excipients [See ]. Warnings and Precautions (5.4)

5. WARNINGS AND PRECAUTIONS

5.1 Dosage adjustment and monitoring

Glucose monitoring is essential for all patients receiving insulin therapy. Changes to an insulin regimen should be made cautiously and only under medical supervision.

Changes in insulin strength, manufacturer, type, or method of administration may result in the need for a change in insulin dose or an adjustment in concomitant oral anti-diabetic treatment.

As with all insulin preparations, the time course of action for LANTUS may vary in different individuals or at different times in the same individual and is dependent on many conditions, including the local blood supply, local temperature, and physical activity.

5.2 Administration

Do not administer LANTUS intravenously or via an insulin pump. The intended duration of activity of LANTUS is dependent on injection into subcutaneous tissue

Intravenous administration of the usual subcutaneous dose could result in severe hypoglycemia . [see ] Warnings and Precautions (5.3)

Do not dilute or mix LANTUS with any other insulin or solution. If LANTUS is diluted or mixed, the solution may become cloudy, and the pharmacokinetic or pharmacodynamic profile (e.g., onset of action, time to peak effect) of LANTUS and the mixed insulin may be altered in an unpredictable manner. When LANTUS and regular human insulin were mixed immediately before injection in dogs, a delayed onset of action and a delayed time to maximum effect for regular human insulin was observed. The total bioavailability of the mixture was also slightly decreased compared to separate injections of LANTUS and regular human insulin. The relevance of these observations in dogs to humans is unknown.

Do not share disposable or reusable insulin devices or needles between patients, because doing so carries a risk for transmission of blood-borne pathogens.

5.3 Hypoglycemia

Hypoglycemia is the most common adverse reaction of insulin, including LANTUS. The risk of hypoglycemia increases with intensive glycemic control. Patients must be educated to recognize and manage hypoglycemia. Severe hypoglycemia can lead to unconsciousness or convulsions and may result in temporary or permanent impairment of brain function or death. Severe hypoglycemia requiring the assistance of another person or parenteral glucose infusion or glucagon administration has been observed in clinical trials with insulin, including trials with LANTUS.

The timing of hypoglycemia usually reflects the time-action profile of the administered insulin formulations. Other factors such as changes in food intake (e.g., amount of food or timing of meals), exercise, and concomitant medications may also alter the risk of hypoglycemia [ ]. See Drug Interactions (7)

The prolonged effect of subcutaneous LANTUS may delay recovery from hypoglycemia. Patients being switched from twice daily NPH insulin to once-daily LANTUS should have their initial LANTUS dose reduced by 20% from the previous total daily NPH dose to reduce the risk of hypoglycemia [see ]. Dosage and Administration (2.3)

As with all insulins, use caution in patients with hypoglycemia unawareness and in patients who may be predisposed to hypoglycemia (e.g., the pediatric population and patients who fast or have erratic food intake). The patient's ability to concentrate and react may be impaired as a result of hypoglycemia. This may present a risk in situations where these abilities are especially important, such as driving or operating other machinery.

Early warning symptoms of hypoglycemia may be different or less pronounced under certain conditions, such as longstanding diabetes, diabetic neuropathy, use of medications such as beta-blockers, or intensified glycemic control. These situations may result in severe hypoglycemia (and, possibly, loss of consciousness) prior to the patient's awareness of hypoglycemia.

5.4 Hypersensitivity and allergic reactions

Severe, life-threatening, generalized allergy, including anaphylaxis, can occur with insulin products, including LANTUS.

5.5 Renal impairment

Due to its long duration of action, Lantus is not recommended during periods of rapidly declining renal function because of the risk for prolonged hypoglycemia.

Although studies have not been performed in patients with diabetes and renal impairment, a reduction in the LANTUS dose may be required in patients with renal impairment because of reduced insulin metabolism, similar to observations found with other insulins. [See ]. Clinical Pharmacology (12.3)

5.6 Hepatic impairment

Due to its long duration of action, Lantus is not recommended during periods of rapidly declining hepatic function because of the risk for prolonged hypoglycemia.

Although studies have not been performed in patients with diabetes and hepatic impairment, a reduction in the LANTUS dose may be required in patients with hepatic impairment because of reduced capacity for gluconeogenesis and reduced insulin metabolism, similar to observations found with other insulins. [See ]. Clinical Pharmacology (12.3)

5.7 Drug interactions

Some medications may alter insulin requirements and subsequently increase the risk for hypoglycemia or hyperglycemia [See ]. Drug Interactions (7)

5.8 Fluid retention and heart failure with concomitant use of PPAR-gamma agonists

Thiazolidinediones (TZDs), which are peroxisome proliferator-activated receptor (PPAR)-gamma agonists, can cause dose-related fluid retention, particularly when used in combination with insulin. Fluid retention may lead to or exacerbate heart failure. Patients treated with insulin, including LANTUS, and a PPAR-gamma agonist should be observed for signs and symptoms of heart failure. If heart failure develops, it should be managed according to current standards of care, and discontinuation or dose reduction of the PPAR-gamma agonist must be considered.

6. ADVERSE REACTIONS

The following adverse reactions are discussed elsewhere:

- Hypoglycemia [See ] Warnings and Precautions (5.3)
- Hypersensitivity and allergic reactions [See ] Warnings and Precautions (5.4)

6.1 Clinical trial experience

Because clinical trials are conducted under widely varying designs, the adverse reaction rates reported in one clinical trial may not be easily compared to those rates reported in another clinical trial, and may not reflect the rates actually observed in clinical practice.

The frequencies of treatment-emergent adverse events during LANTUS clinical trials in patients with type 1 diabetes mellitus and type 2 diabetes mellitus are listed in the tables below.

Table 1: Treatment –emergent adverse events in pooled clinical trials up to 28 weeks duration in adults with type 1 diabetes (adverse events with frequency ≥ 5%)
 | LANTUS, % (n=1257) | NPH, % (n=1070)
Upper respiratory tract infection | 22.4 | 23.1
Infection [Body System not Specified] | 9.4 | 10.3
Accidental injury | 5.7 | 6.4
Headache | 5.5 | 4.7

Table 2: Treatment –emergent adverse events in pooled clinical trials up to 1 year duration in adults with type 2 diabetes (adverse events with frequency ≥ 5%)
 | LANTUS, % (n=849) | NPH, % (n=714)
Upper respiratory tract infection | 11.4 | 13.3
Infection [Body System not Specified] | 10.4 | 11.6
Retinal vascular disorder | 5.8 | 7.4

Table 3: Treatment –emergent adverse events in a 5-year trial of adults with type 2 diabetes (adverse events with frequency ≥ 10%)
 | LANTUS, % (n=514) | NPH, % (n=503)
Upper respiratory tract infection | 29.0 | 33.6
Edema peripheral | 20.0 | 22.7
Hypertension | 19.6 | 18.9
Influenza | 18.7 | 19.5
Sinusitis | 18.5 | 17.9
Cataract | 18.1 | 15.9
Bronchitis | 15.2 | 14.1
Arthralgia | 14.2 | 16.1
Pain in extremity | 13.0 | 13.1
Back pain | 12.8 | 12.3
Cough | 12.1 | 7.4
Urinary tract infection | 10.7 | 10.1
Diarrhea | 10.7 | 10.3
Depression | 10.5 | 9.7
Headache | 10.3 | 9.3

Table 4: Treatment –emergent adverse events in a 28-week clinical trial of children and adolescents with type 1 diabetes (adverse events with frequency ≥ 5%)
 | LANTUS, % (n=174) | NPH, % (n=175)
Infection [Body System not Specified] | 13.8 | 17.7
Upper respiratory tract infection | 13.8 | 16.0
Pharyngitis | 7.5 | 8.6
Rhinitis | 5.2 | 5.1

- Severe Hypoglycemia

Hypoglycemia is the most commonly observed adverse reaction in patients using insulin, including LANTUS . Tables 5, and 6 and 7 summarize the incidence of severe hypoglycemia in the LANTUS individual clinical trials. Severe symptomatic hypoglycemia was defined as an event with symptoms consistent with hypoglycemia requiring the assistance of another person and associated with either a blood glucose below 50 mg/dL (≤56 mg/dL in the 5-year trial and ≤36 mg/dL in the ORIGIN trial) or prompt recovery after oral carbohydrate, intravenous glucose or glucagon administration. [See ] Warnings and Precautions (5.3)

The proportion of patients experiencing severe symptomatic hypoglycemia in the LANTUS clinical trials [ ] in adults with type 1 diabetes and type 2 diabetes were comparable for all treatment regimens (see and). In the pediatric phase 3 clinical trial, children and adolescents with type 1 diabetes had a higher incidence of severe symptomatic hypoglycemia in the two treatment groups compared to the adult trials with type 1 diabetes. See Clinical Studies (14) Tables 56

Table 5: Severe Symptomatic Hypoglycemia in Patients with Type 1 Diabetes
 | Study A Type 1 Diabetes Adults 28 weeks In combination with regular insulin |  | Study B Type 1 Diabetes Adults 28 weeks In combination with regular insulin |  | Study C Type 1 Diabetes Adults 16 weeks In combination with insulin lispro |  | Study D Type 1 Diabetes Pediatrics 26 weeks In combination with regular insulin
 | LANTUS | NPH | LANTUS | NPH | LANTUS | NPH | LANTUS | NPH
Percent of patients (n/total N) | 10.6 (31/292) | 15.0 (44/293) | 8.7 (23/264) | 10.4 (28/270) | 6.5 (20/310) | 5.2 (16/309) | 23.0 (40/174) | 28.6 (50/175)

Table 6: Severe Symptomatic Hypoglycemia in Patients with Type 2 Diabetes
 | Study E Type 2 Diabetes Adults 52 weeks In combination with oral agents |  | Study F Type 2 Diabetes Adults 28 weeks In combination with regular insulin |  | Study G Type 2 Diabetes Adults 5 years In combination with regular insulin
 | LANTUS | NPH | LANTUS | NPH | LANTUS | NPH
Percent of patients (n/total N) | 1.7 (5/289) | 1.1 (3/281) | 0.4 (1/259) | 2.3 (6/259) | 7.8 (40/513) | 11.9 (60/504)

Table 7 displays the proportion of patients experiencing severe symptomatic hypoglycemia in the Lantus and Standard Care groups in the ORIGIN Trial [ ]. see Adverse Reactions (cardiovascular safety)

Table 7: Severe Symptomatic Hypoglycemia in the ORIGIN trial
 | Median duration of follow-up: 6.2 years ORIGIN Trial
 | LANTUS | Standard Care
Percent of patients (n/total N) | 5.6 (352/6231) | 1.8 (113/6273)

- Retinopathy

Retinopathy was evaluated in the LANTUS clinical studies by analysis of reported retinal adverse events and fundus photography. The numbers of retinal adverse events reported for LANTUS and NPH insulin treatment groups were similar for patients with type 1 and type 2 diabetes.

LANTUS was compared to NPH insulin in a 5-year randomized clinical trial that evaluated the progression of retinopathy as assessed with fundus photography using a grading protocol derived from the Early Treatment Diabetic Retinopathy Scale (ETDRS). Patients had type 2 diabetes (mean age 55 yrs) with no (86%) or mild (14%) retinopathy at baseline. Mean baseline HbA1c was 8.4%. The primary outcome was progression by 3 or more steps on the ETDRS scale at study endpoint. Patients with pre-specified post-baseline eye procedures (pan-retinal photocoagulation for proliferative or severe nonproliferative diabetic retinopathy, local photocoagulation for new vessels, and vitrectomy for diabetic retinopathy) were also considered as 3-step progressors regardless of actual change in ETDRS score from baseline. Retinopathy graders were blinded to treatment group assignment. The results for the primary endpoint are shown in Table 8 for both the per-protocol and Intent-to-Treat populations, and indicate similarity of Lantus to NPH in the progression of diabetic retinopathy as assessed by this outcome.

Table 8: Number (%) of patients with 3 or more step progression on ETDRS scale at endpoint
 | Lantus (%) | NPH (%) | Difference (SE) [Difference = Lantus – NPH] , [using a generalized linear model (SAS GENMOD) with treatment and baseline HbA1c strata (cutoff 9.0%) as the classified independent variables, and with binomial distribution and identity link function] | 95% CI for difference
Per-protocol | 53/374 (14.2%) | 57/363 (15.7%) | -2.0% (2.6%) | -7.0% to +3.1%
Intent-to-Treat | 63/502 (12.5%) | 71/487 (14.6%) | - 2.1% (2.1%) | -6.3% to +2.1%

- Insulin initiation and intensification of glucose control

Intensification or rapid improvement in glucose control has been associated with a transitory, reversible ophthalmologic refraction disorder, worsening of diabetic retinopathy, and acute painful peripheral neuropathy. However, long-term glycemic control decreases the risk of diabetic retinopathy and neuropathy.

- Lipodystrophy

Long-term use of insulin, including LANTUS, can cause lipodystrophy at the site of repeated insulin injections. Lipodystrophy includes lipohypertrophy (thickening of adipose tissue) and lipoatrophy (thinning of adipose tissue), and may affect insulin absorption. Rotate insulin injection or infusion sites within the same region to reduce the risk of lipodystrophy. [See ]. Dosage and Administration (2.1)

- Weight gain

Weight gain can occur with insulin therapy, including LANTUS, and has been attributed to the anabolic effects of insulin and the decrease in glucosuria.

- Peripheral Edema

Insulin, including LANTUS, may cause sodium retention and edema, particularly if previously poor metabolic control is improved by intensified insulin therapy.

- Allergic Reactions

Local Allergy

As with any insulin therapy, patients taking LANTUS may experience injection site reactions, including redness, pain, itching, urticaria, edema, and inflammation. In clinical studies in adult patients, there was a higher incidence of treatment-emergent injection site pain in LANTUS-treated patients (2.7%) compared to NPH insulin-treated patients (0.7%). The reports of pain at the injection site did not result in discontinuation of therapy.

Rotation of the injection site within a given area from one injection to the next may help to reduce or prevent these reactions. In some instances, these reactions may be related to factors other than insulin, such as irritants in a skin cleansing agent or poor injection technique. Most minor reactions to insulin usually resolve in a few days to a few weeks.

Systemic Allergy

Severe, life-threatening, generalized allergy, including anaphylaxis, generalized skin reactions, angioedema, bronchospasm, hypotension, and shock may occur with any insulin, including LANTUS and may be life threatening.

- Antibody production

All insulin products can elicit the formation of insulin antibodies. The presence of such insulin antibodies may increase or decrease the efficacy of insulin and may require adjustment of the insulin dose. In phase 3 clinical trials of LANTUS, increases in titers of antibodies to insulin were observed in NPH insulin and insulin glargine treatment groups with similar incidences.

- Cardiovascular Safety

The Outcome Reduction with Initial Glargine Intervention trial (i.e., ORIGIN) was an open-label, randomized, 2-by-2, factorial design study. One intervention in ORIGIN compared the effect of LANTUS to standard care on major adverse cardiovascular outcomes in 12,537 participants ≥ 50 years of age with abnormal glucose levels [i.e., impaired fasting glucose (IFG) and/or impaired glucose tolerance (IGT)] or early type 2 diabetes mellitus and established cardiovascular (i.e., CV) disease or CV risk factors at baseline.

The objective of the trial was to demonstrate that LANTUS use could significantly lower the risk of major cardiovascular outcomes compared to standard care. Two co-primary composite cardiovascular endpoints were used in ORIGIN. The first co-primary endpoint was the time to first occurrence of a major adverse cardiovascular event defined as the composite of CV death, nonfatal myocardial infarction and nonfatal stroke. The second co-primary endpoint was the time to the first occurrence of CV death or nonfatal myocardial infarction or nonfatal stroke or revascularization procedure or hospitalization for heart failure.

Participants were randomized to either LANTUS (N=6264) titrated to a goal fasting plasma glucose of ≤ 95 mg/dL or to standard care (N=6273). Anthropometric and disease characteristics were balanced at baseline. The mean age was 64 years and 8% of participants were 75 years of age or older. The majority of participants were male (65%). Fifty nine percent were Caucasian, 25% were Latin, 10% were Asian and 3% were Black. The median baseline BMI was 29 kg/m . Approximately 12% of participants had abnormal glucose levels (IGT and/or IFG) at baseline and 88% had type 2 diabetes. For patients with type 2 diabetes, 59% were treated with a single oral antidiabetic drug, 23% had known diabetes but were on no antidiabetic drug and 6% were newly diagnosed during the screening procedure. The mean HbA1c (SD) at baseline was 6.5% (1.0). Fifty nine percent of participants had had a prior cardiovascular event and 39% had documented coronary artery disease or other cardiovascular risk factors.^2

Vital status was available for 99.9% and 99.8% of participants randomized to LANTUS and standard care respectively at end of trial. The median duration of follow-up was 6.2 years [range: 8 days to 7.9 years]. The mean HbA1c (SD) at the end of the trial was 6.5% (1.1) and 6.8% (1.2) in the LANTUS and standard care group respectively. The median dose of LANTUS at end of trial was 0.45 U/kg. Eighty-one percent of patients randomized to LANTUS were using LANTUS at end of the study. The mean change in body weight from baseline to the last treatment visit was 2.2 kg greater in the LANTUS group than in the standard care group.

Overall, the incidence of major adverse cardiovascular outcomes was similar between groups (see). All-cause mortality was also similar between groups. Table 9

Table 9: Cardiovascular Outcomes in ORIGIN - Time to First Event Analyses
 | LANTUS N=6264 | Standard Care N=6273 | LANTUS vs Standard Care
 | n (Events per 100 PY) | n (Events per 100 PY) | Hazard Ratio (95% CI)
Co-primary endpoints
CV death, nonfatal myocardial infarction, or nonfatal stroke | 1041 (2.9) | 1013 (2.9) | 1.02 (0.94, 1.11)
CV death, nonfatal myocardial infarction, nonfatal stroke, hospitalization for heart failure or revascularization procedure | 1792 (5.5) | 1727 (5.3) | 1.04 (0.97, 1.11)
Components of co-primary endpoints
CV death | 580 | 576 | 1.00 (0.89, 1.13)
Myocardial Infarction (fatal or non-fatal) | 336 | 326 | 1.03 (0.88, 1.19)
Stroke (fatal or non-fatal) | 331 | 319 | 1.03 (0.89, 1.21)
Revascularizations | 908 | 860 | 1.06 (0.96, 1.16)
Hospitalization for heart failure | 310 | 343 | 0.90 (0.77, 1.05)

- Cancer

In the ORIGIN trial, the overall incidence of cancer (all types combined) or death from cancer (Table 10) was similar between treatment groups.

Table 10: Cancer Outcomes in ORIGIN - Time to First Event Analyses
 | LANTUS N=6264 | Standard Care N=6273 | LANTUS vs Standard Care
 | n (Events per 100 PY) | n (Events per 100 PY) | Hazard Ratio (95% CI)
Cancer endpoints
Any cancer event (new or recurrent) | 559 (1.56) | 561 (1.56) | 0.99 (0.88, 1.11)
New cancer events | 524 (1.46) | 535 (1.49) | 0.96 (0.85, 1.09)
Death due to Cancer | 189 (0.51) | 201 (0.54) | 0.94 (0.77, 1.15)

6.2 Postmarketing experience

The following adverse reactions have been identified during post-approval use of LANTUS.

Because these reactions are reported voluntarily from a population of uncertain size, it is not always possible to estimate reliably their frequency or establish a causal relationship to drug exposure.

Medication errors have been reported in which other insulins, particularly short-acting insulins, have been accidentally administered instead of LANTUS ]. To avoid medication errors between LANTUS and other insulins, patients should be instructed to always verify the insulin label before each injection. [See Patient Counseling Information (17)

7. DRUG INTERACTIONS

A number of drugs affect glucose metabolism and may require insulin dose adjustment and particularly close monitoring.

The following are examples of drugs that may increase the blood-glucose-lowering effect of insulins including LANTUS and, therefore, increase the susceptibility to hypoglycemia: oral anti-diabetic products, pramlintide, angiotensin converting enzyme (ACE) inhibitors, disopyramide, fibrates, fluoxetine, monoamine oxidase inhibitors, propoxyphene, pentoxifylline, salicylates, somatostatin analogs, and sulfonamide antibiotics.

The following are examples of drugs that may reduce the blood-glucose-lowering effect of insulins including LANTUS: corticosteroids, niacin, danazol, diuretics, sympathomimetic agents (e.g., epinephrine, albuterol, terbutaline), glucagon, isoniazid, phenothiazine derivatives, somatropin, thyroid hormones, estrogens, progestogens (e.g., in oral contraceptives), protease inhibitors and atypical antipsychotic medications (e.g. olanzapine and clozapine).

Beta-blockers, clonidine, lithium salts, and alcohol may either potentiate or weaken the blood-glucose-lowering effect of insulin. Pentamidine may cause hypoglycemia, which may sometimes be followed by hyperglycemia.

The signs of hypoglycemia may be reduced or absent in patients taking sympatholytic drugs such as beta-blockers, clonidine, guanethidine, and reserpine.

8. USE IN SPECIFIC POPULATIONS

8.1 Pregnancy

TERATOGENIC EFFECTS

Pregnancy Category C: Subcutaneous reproduction and teratology studies have been performed with insulin glargine and regular human insulin in rats and Himalayan rabbits. Insulin glargine was given to female rats before mating, during mating, and throughout pregnancy at doses up to 0.36 mg/kg/day, which is approximately 7 times the recommended human subcutaneous starting dose of 10 Units/day (0.008 mg/kg/day), based on mg/m . In rabbits, doses of 0.072 mg/kg/day, which is approximately 2 times the recommended human subcutaneous starting dose of 10 Units/day (0.008 mg/kg/day), based on mg/m , were administered during organogenesis. The effects of insulin glargine did not generally differ from those observed with regular human insulin in rats or rabbits. However, in rabbits, five fetuses from two litters of the high-dose group exhibited dilation of the cerebral ventricles. Fertility and early embryonic development appeared normal.^2^2

There are no well-controlled clinical studies of the use of LANTUS in pregnant women. Because animal reproduction studies are not always predictive of human response, this drug should be used during pregnancy only if the potential benefit justifies the potential risk to the fetus. It is essential for patients with diabetes or a history of gestational diabetes to maintain good metabolic control before conception and throughout pregnancy. Insulin requirements may decrease during the first trimester, generally increase during the second and third trimesters, and rapidly decline after delivery. Careful monitoring of glucose control is essential in these patients.

8.3 Nursing Mothers

It is unknown whether insulin glargine is excreted in human milk. Because many drugs, including human insulin, are excreted in human milk, caution should be exercised when LANTUS is administered to a nursing woman. Use of LANTUS is compatible with breastfeeding, but women with diabetes who are lactating may require adjustments of their insulin doses.

8.4 Pediatric Use

The safety and effectiveness of subcutaneous injections of LANTUS have been established in pediatric patients (age 6 to 15 years) with type 1 diabetes . LANTUS has not been studied in pediatric patients younger than 6 years of age with type 1 diabetes. LANTUS has not been studied in pediatric patients with type 2 diabetes. [see ] Clinical Studies (14)

Based on the results of a study in pediatric patients, the dose recommendation when switching to LANTUS is the same as that described for adults and As in adults, the dosage of LANTUS must be individualized in pediatric patients based on metabolic needs and frequent monitoring of blood glucose. [see Dosage and Administration (2.3)]. Clinical Studies (14)

8.5 Geriatric Use

In controlled clinical studies comparing LANTUS to NPH insulin, 593 of 3890 patients (15%) with type 1 and type 2 diabetes were ≥65 years of age and 80 (2%) patients were ≥75 years of age. The only difference in safety or effectiveness in the subpopulation of patients ≥65 years of age compared to the entire study population was a higher incidence of cardiovascular events typically seen in an older population in both LANTUS and NPH insulin-treated patients.

Nevertheless, caution should be exercised when LANTUS is administered to geriatric patients. In elderly patients with diabetes, the initial dosing, dose increments, and maintenance dosage should be conservative to avoid hypoglycemic reactions. Hypoglycemia may be difficult to recognize in the elderly [See ]. Warnings and Precautions (5.3)

10. OVERDOSAGE

An excess of insulin relative to food intake, energy expenditure, or both may lead to severe and sometimes prolonged and life-threatening hypoglycemia. Mild episodes of hypoglycemia can usually be treated with oral carbohydrates. Adjustments in drug dosage, meal patterns, or exercise may be needed.

More severe episodes of hypoglycemia with coma, seizure, or neurologic impairment may be treated with intramuscular/subcutaneous glucagon or concentrated intravenous glucose. After apparent clinical recovery from hypoglycemia, continued observation and additional carbohydrate intake may be necessary to avoid recurrence of hypoglycemia.

11. DESCRIPTION

LANTUS (insulin glargine [rDNA origin] injection) is a sterile solution of insulin glargine for use as a subcutaneous injection. Insulin glargine is a recombinant human insulin analog that is a long-acting (up to 24-hour duration of action), parenteral blood-glucose-lowering agent [ ]. LANTUS is produced by recombinant DNA technology utilizing a non-pathogenic laboratory strain of (K12) as the production organism. Insulin glargine differs from human insulin in that the amino acid asparagine at position A21 is replaced by glycine and two arginines are added to the C-terminus of the B-chain. Chemically, insulin glargine is 21 -Gly-30 a-L-Arg-30 b-L-Arg-human insulin and has the empirical formula C H N O S and a molecular weight of 6063. Insulin glargine has the following structural formula: See Clinical Pharmacology (12) Escherichia coliABB26740472786

LANTUS consists of insulin glargine dissolved in a clear aqueous fluid. Each milliliter of LANTUS (insulin glargine injection) contains 100 Units (3.6378 mg) insulin glargine.

The 10 mL vial presentation contains the following inactive ingredients per mL: 30 mcg zinc, 2.7 mg m-cresol, 20 mg glycerol 85%, 20 mcg polysorbate 20, and water for injection.

The 3 mL cartridge presentation contains the following inactive ingredients per mL: 30 mcg zinc, 2.7 mg m-cresol, 20 mg glycerol 85%, and water for injection.

The pH is adjusted by addition of aqueous solutions of hydrochloric acid and sodium hydroxide. LANTUS has a pH of approximately 4.

12. CLINICAL PHARMACOLOGY

12.1 Mechanism of Action

The primary activity of insulin, including insulin glargine, is regulation of glucose metabolism. Insulin and its analogs lower blood glucose by stimulating peripheral glucose uptake, especially by skeletal muscle and fat, and by inhibiting hepatic glucose production. Insulin inhibits lipolysis and proteolysis, and enhances protein synthesis.

12.2 Pharmacodynamics

Insulin glargine is a human insulin analog that has been designed to have low aqueous solubility at neutral pH. At pH 4, as in the LANTUS injection solution, insulin glargine is completely soluble. After injection into the subcutaneous tissue, the acidic solution is neutralized, leading to formation of microprecipitates from which small amounts of insulin glargine are slowly released, resulting in a relatively constant concentration/time profile over 24 hours with no pronounced peak. This profile allows once-daily dosing as a basal insulin.

In clinical studies, the glucose-lowering effect on a molar basis (i.e., when given at the same doses) of intravenous insulin glargine is approximately the same as that for human insulin. In euglycemic clamp studies in healthy subjects or in patients with type 1 diabetes, the onset of action of subcutaneous insulin glargine was slower than NPH insulin. The effect profile of insulin glargine was relatively constant with no pronounced peak and the duration of its effect was prolonged compared to NPH insulin. shows results from a study in patients with type 1 diabetes conducted for a maximum of 24 hours after the injection. The median time between injection and the end of pharmacological effect was 14.5 hours (range: 9.5 to 19.3 hours) for NPH insulin, and 24 hours (range: 10.8 to >24.0 hours) (24 hours was the end of the observation period) for insulin glargine. Figure 1

Figure 1. Activity Profile in Patients with Type 1 Diabetes

* Determined as amount of glucose infused to maintain constant plasma glucose levels (hourly mean values); indicative of insulin activity.

The longer duration of action (up to 24 hours) of LANTUS is directly related to its slower rate of absorption and supports once-daily subcutaneous administration. The time course of action of insulins, including LANTUS, may vary between individuals and within the same individual.

12.3 Pharmacokinetics

Absorption and Bioavailability. After subcutaneous injection of insulin glargine in healthy subjects and in patients with diabetes, the insulin serum concentrations indicated a slower, more prolonged absorption and a relatively constant concentration/time profile over 24 hours with no pronounced peak in comparison to NPH insulin. Serum insulin concentrations were thus consistent with the time profile of the pharmacodynamic activity of insulin glargine.

After subcutaneous injection of 0.3 Units/kg insulin glargine in patients with type 1 diabetes, a relatively constant concentration/time profile has been demonstrated. The duration of action after abdominal, deltoid, or thigh subcutaneous administration was similar.

Metabolism. A metabolism study in humans indicates that insulin glargine is partly metabolized at the carboxyl terminus of the B chain in the subcutaneous depot to form two active metabolites with in vitro activity similar to that of insulin, M1 (21 -Gly-insulin) and M2 (21 -Gly-des-30 -Thr-insulin). Unchanged drug and these degradation products are also present in the circulation.AAB

Special Populations

Information on the effect of age, race, and gender on the pharmacokinetics of LANTUS is not available. However, in controlled clinical trials in adults (n=3890) and a controlled clinical trial in pediatric patients (n=349), subgroup analyses based on age, race, and gender did not show differences in safety and efficacy between insulin glargine and NPH insulin . Age, Race, and Gender.[see ] Clinical Studies (14)

The effect of smoking on the pharmacokinetics/pharmacodynamics of LANTUS has not been studied. Smoking.

The effect of pregnancy on the pharmacokinetics and pharmacodynamics of LANTUS has not been studied [ Pregnancy. see ]. Use in Specific Populations (8.1)

. In controlled clinical trials, which included patients with Body Mass Index (BMI) up to and including 49.6 kg/m , subgroup analyses based on BMI did not show differences in safety and efficacy between insulin glargine and NPH insulin . Obesity^2 [see ] Clinical Studies (14)

The effect of renal impairment on the pharmacokinetics of LANTUS has not been studied. However, some studies with human insulin have shown increased circulating levels of insulin in patients with renal failure. Careful glucose monitoring and dose adjustments of insulin, including LANTUS, may be necessary in patients with renal impairment S Renal Impairment.[ee ]. Warnings and Precautions (5.5)

. The effect of hepatic impairment on the pharmacokinetics of LANTUS has not been studied. However, some studies with human insulin have shown increased circulating levels of insulin in patients with liver failure. Careful glucose monitoring and dose adjustments of insulin, including LANTUS, may be necessary in patients with hepatic impairment Hepatic Impairment [See ]. Warnings and Precautions (5.6)

13. NONCLINICAL TOXICOLOGY

13.1 Carcinogenesis, Mutagenesis, Impairment of Fertility

In mice and rats, standard two-year carcinogenicity studies with insulin glargine were performed at doses up to 0.455 mg/kg, which was for the rat approximately 10 times and for the mouse approximately 5 times the recommended human subcutaneous starting dose of 10 Units/day (0.008 mg/kg/day), based on mg/m . The findings in female mice were not conclusive due to excessive mortality in all dose groups during the study. Histiocytomas were found at injection sites in male rats (statistically significant) and male mice (not statistically significant) in acid vehicle containing groups. These tumors were not found in female animals, in saline control, or insulin comparator groups using a different vehicle. The relevance of these findings to humans is unknown.^2

Insulin glargine was not mutagenic in tests for detection of gene mutations in bacteria and mammalian cells (Ames- and HGPRT-test) and in tests for detection of chromosomal aberrations (cytogenetics in vitro in V79 cells and in vivo in Chinese hamsters).

In a combined fertility and prenatal and postnatal study in male and female rats at subcutaneous doses up to 0.36 mg/kg/day, which was approximately 7 times the recommended human subcutaneous starting dose of 10 Units/day (0.008 mg/kg/day), based on mg/m , maternal toxicity due to dose-dependent hypoglycemia, including some deaths, was observed. Consequently, a reduction of the rearing rate occurred in the high-dose group only. Similar effects were observed with NPH insulin.^2

14. CLINICAL STUDIES

The safety and effectiveness of LANTUS given once-daily at bedtime was compared to that of once-daily and twice-daily NPH insulin in open-label, randomized, active-controlled, parallel studies of 2,327 adult patients and 349 pediatric patients with type 1 diabetes mellitus and 1,563 adult patients with type 2 diabetes mellitus (see Tables 9–11), In general, the reduction in glycated hemoglobin (HbA1c) with LANTUS was similar to that with NPH insulin. The overall rates of hypoglycemia did not differ between patients with diabetes treated with LANTUS compared to NPH insulin . [See ] Adverse Reactions (6.1)

(see). Type 1 Diabetes–Adult Table 11

In two clinical studies (Studies A and B), patients with type 1 diabetes (Study A; n=585, Study B; n=534) were randomized to 28 weeks of basal-bolus treatment with LANTUS or NPH insulin. Regular human insulin was administered before each meal. LANTUS was administered at bedtime. NPH insulin was administered once daily at bedtime or in the morning and at bedtime when used twice daily.

In another clinical study (Study C), patients with type 1 diabetes (n=619) were randomized to 16 weeks of basal-bolus treatment with LANTUS or NPH insulin. Insulin lispro was used before each meal. LANTUS was administered once daily at bedtime and NPH insulin was administered once or twice daily.

In these 3 studies, LANTUS and NPH insulin had similar effects on HbA1c (Table 11) with a similar overall rate of hypoglycemia . [See ] Adverse Reactions (6.1)

Table 11: Type 1 Diabetes Mellitus–Adult
 | Study A |  | Study B |  | Study C
Treatment duration Treatment in combination with | 28 weeks Regular insulin |  | 28 weeks Regular insulin |  | 16 weeks Insulin lispro
 | LANTUS | NPH | LANTUS | NPH | LANTUS | NPH
Number of subjects treated | 292 | 293 | 264 | 270 | 310 | 309
HbA1c
Baseline HbA1c | 8.0 | 8.0 | 7.7 | 7.7 | 7.6 | 7.7
Adj. mean change from baseline | +0.2 | +0.1 | -0.2 | -0.2 | -0.1 | -0.1
LANTUS – NPH | +0.1 |  | +0.1 |  | 0.0
95% CI for Treatment difference | (0.0; +0.2) |  | (-0.1; +0.2) |  | (-0.1; +0.1)
Basal insulin dose
Baseline mean | 21 | 23 | 29 | 29 | 28 | 28
Mean change from baseline | -2 | 0 | -4 | +2 | -5 | +1
Total insulin dose
Baseline mean | 48 | 52 | 50 | 51 | 50 | 50
Mean change from baseline | -1 | 0 | 0 | +4 | -3 | 0
Fasting blood glucose (mg/dL)
Baseline mean | 167 | 166 | 166 | 175 | 175 | 173
Adj. mean change from baseline | -21 | -16 | -20 | -17 | -29 | -12
Body weight (kg)
Baseline mean | 73.2 | 74.8 | 75.5 | 75.0 | 74.8 | 75.6
Mean change from baseline | 0.1 | -0.0 | 0.7 | 1.0 | 0.1 | 0.5

Type 1 Diabetes–Pediatric (see). Table 12

In a randomized, controlled clinical study (Study D), pediatric patients (age range 6 to 15 years) with type 1 diabetes (n=349) were treated for 28 weeks with a basal-bolus insulin regimen where regular human insulin was used before each meal. LANTUS was administered once daily at bedtime and NPH insulin was administered once or twice daily. Similar effects on HbA1c (Table 12) and the incidence of hypoglycemia were observed in both treatment groups . [See ] Adverse Reactions (6.1)

Table 12: Type 1 Diabetes Mellitus–Pediatric
 | Study D
Treatment duration | 28 weeks
Treatment in combination with | Regular insulin
 | LANTUS | NPH
Number of subjects treated | 174 | 175
HbA1c
Baseline mean | 8.5 | 8.8
Adj. mean change from baseline | +0.3 | +0.3
LANTUS – NPH | 0.0
95% CI for Treatment difference | (-0.2; +0.3)
Basal insulin dose
Baseline mean | 19 | 19
Mean change from baseline | -1 | +2
Total insulin dose
Baseline mean | 43 | 43
Mean change from baseline | +2 | +3
Fasting blood glucose (mg/dL)
Baseline mean | 194 | 191
Adj. mean change from baseline | -23 | -12
Body weight (kg)
Baseline mean | 45.5 | 44.6
Mean change from baseline | 2.2 | 2.5

Type 2 Diabetes–Adult (see). Table 13

In a randomized, controlled clinical study (Study E) (n=570), LANTUS was evaluated for 52 weeks in combination with oral anti-diabetic medications (a sulfonylurea, metformin, acarbose, or combinations of these drugs). LANTUS administered once daily at bedtime was as effective as NPH insulin administered once daily at bedtime in reducing HbA1c and fasting glucose (Table 13). The rate of hypoglycemia was similar in LANTUS and NPH insulin treated patients . [See ] Adverse Reactions (6.1)

In a randomized, controlled clinical study (Study F), in patients with type 2 diabetes not using oral anti-diabetic medications (n=518), a basal-bolus regimen of LANTUS once daily at bedtime or NPH insulin administered once or twice daily was evaluated for 28 weeks. Regular human insulin was used before meals, as needed. LANTUS had similar effectiveness as either once- or twice-daily NPH insulin in reducing HbA1c and fasting glucose (Table 13) with a similar incidence of hypoglycemia . [See ] Adverse Reactions (6.1)

In a randomized, controlled clinical study (Study G), patients with type 2 diabetes were randomized to 5 years of treatment with once-daily LANTUS or twice-daily NPH insulin. For patients not previously treated with insulin, the starting dose of LANTUS or NPH insulin was 10 units daily. Patients who were already treated with NPH insulin either continued on the same total daily NPH insulin dose or started LANTUS at a dose that was 80% of the total previous NPH insulin dose. The primary endpoint for this study was a comparison of the progression of diabetic retinopathy by 3 or more steps on the Early Treatment Diabetic Retinopathy Study (ETDRS) scale. HbA1c change from baseline was a secondary endpoint. Similar glycemic control in the 2 treatment groups was desired in order to not confound the interpretation of the retinal data. Patients or study personnel used an algorithm to adjust the LANTUS and NPH insulin doses to a target fasting plasma glucose ≤100 mg/dL. After the LANTUS or NPH insulin dose was adjusted, other anti-diabetic agents, including pre-meal insulin were to be adjusted or added. The LANTUS group had a smaller mean reduction from baseline in HbA1c compared to the NPH insulin group, which may be explained by the lower daily basal insulin doses in the LANTUS group (Table 13). Both treatment groups had a similar incidence of reported symptomatic hypoglycemia. The incidences of severe symptomatic hypoglycemia are given in Table 6 . [See ] Adverse Reactions (6.1)

Table 13: Type 2 Diabetes Mellitus–Adult
 | Study E |  | Study F |  | Study G
Treatment duration | 52 weeks |  | 28 weeks |  | 5 years
Treatment in combination with | Oral agents |  | Regular insulin |  | Regular insulin
 | LANTUS | NPH | LANTUS | NPH | LANTUS | NPH
Number of subjects treated | 289 | 281 | 259 | 259 | 513 | 504
HbA1c
Baseline mean | 9.0 | 8.9 | 8.6 | 8.5 | 8.4 | 8.3
Adj. mean change from baseline | -0.5 | -0.4 | -0.4 | -0.6 | -0.6 | -0.8
LANTUS – NPH | -0.1 |  | +0.2 |  | +0.2
95% CI for Treatment difference | (-0.3; +0.1) |  | (0.0; +0.4) |  | (+0.1, +0.4)
Basal insulin dose [In Study G, the baseline dose of basal or total insulin was the first available on-treatment dose prescribed during the study (on visit month 1.5).]
Baseline mean | 14 | 15 | 44.1 | 45.5 | 39 | 44
Mean change from baseline | +12 | +9 | -1 | +7 | +23 | +30
Total insulin dose
Baseline mean | 14 | 15 | 64 | 67 | 48 | 53
Mean change from baseline | +12 | +9 | +10 | +13 | +41 | +40
Fasting blood glucose (mg/dL)
Baseline mean | 179 | 180 | 164 | 166 | 190 | 180
Adj. mean change from baseline | -49 | -46 | -24 | -22 | -45 | -44
Body weight (kg)
Baseline mean | 83.5 | 82.1 | 89.6 | 90.7 | 100 | 99
Adj. mean change from baseline | 2.0 | 1.9 | 0.4 | 1.4 | 3.7 | 4.8

LANTUS Timing of Daily Dosing (see). Table 14

The safety and efficacy of LANTUS administered pre-breakfast, pre-dinner, or at bedtime were evaluated in a randomized, controlled clinical study in patients with type 1 diabetes (study H, n=378). Patients were also treated with insulin lispro at mealtime. LANTUS administered at different times of the day resulted in similar reductions in HbA1c compared to that with bedtime administration (see). In these patients, data are available from 8-point home glucose monitoring. The maximum mean blood glucose was observed just prior to injection of LANTUS regardless of time of administration. Table 14

In this study, 5% of patients in the LANTUS-breakfast arm discontinued treatment because of lack of efficacy. No patients in the other two arms discontinued for this reason. The safety and efficacy of LANTUS administered pre-breakfast or at bedtime were also evaluated in a randomized, active-controlled clinical study (Study I, n=697) in patients with type 2 diabetes not adequately controlled on oral anti-diabetic therapy. All patients in this study also received glimepiride 3 mg daily. LANTUS given before breakfast was at least as effective in lowering HbA1c as LANTUS given at bedtime or NPH insulin given at bedtime (see). Table 14

Table 14: LANTUS Timing of Daily Dosing in Type 1 (Study H) and Type 2 (Study I) Diabetes Mellitus
 | Study H |  |  | Study I
Treatment duration | 24 weeks |  |  | 24 weeks
Treatment in combination with: | Insulin lispro |  |  | Glimepiride
 | LANTUS Breakfast | LANTUS Dinner | LANTUS Bedtime | LANTUS Breakfast | LANTUS Bedtime | NPH Bedtime
Number of subjects treated [Intent to treat] | 112 | 124 | 128 | 234 | 226 | 227
HbA1c
Baseline mean | 7.6 | 7.5 | 7.6 | 9.1 | 9.1 | 9.1
Mean change from baseline | -0.2 | -0.1 | 0.0 | -1.3 | -1.0 | -0.8
Basal insulin dose (U)
Baseline mean | 22 | 23 | 21 | 19 | 20 | 19
Mean change from baseline | 5 | 2 | 2 | 11 | 18 | 18
Total insulin dose (U) |  |  |  | NA [Not applicable] | NA | NA
Baseline mean | 52 | 52 | 49
Mean change from baseline | 2 | 3 | 2
Body weight (kg)
Baseline mean | 77.1 | 77.8 | 74.5 | 80.7 | 82 | 81
Mean change from baseline | 0.7 | 0.1 | 0.4 | 3.9 | 3.7 | 2.9
**total number of patients evaluable for safety

16. HOW SUPPLIED/STORAGE AND HANDLING

NDC:64725-2220-1 in a VIAL, GLASS of 10 INJECTION, SOLUTIONS

16.1 How supplied

LANTUS solution for injection 100 units per mL (U-100) is available as:

Dosage Unit/Strength | Package size | NDC # 0088
100 Units/mL 10 mL vials | Pack of 1 | 2220-33
100 Units/mL 3 mL SoloStar disposable insulin device® | package of 5 | 2219-05

Needles are not included in the packs.

BD Ultra-Fine™ needles to be used in conjunction with SoloStar are sold separately and are manufactured by BD. [The brands listed are the registered trademarks of their respective owners and are not trademarks of sanofi-aventis U.S. LLC]

16.2 Storage

LANTUS should not be stored in the freezer and should not be allowed to freeze. Discard LANTUS if it has been frozen.

Unopened Vial/ SoloStar disposable insulin device:

Unopened LANTUS vials, cartridge systems and SoloStar device should be stored in a refrigerator, 36°F – 46°F (2°C – 8°C). Discard after the expiration date.

Open (In-Use) Vial:

Vials must be discarded 28 days after being opened. If refrigeration is not possible, the open vial can be kept unrefrigerated for up to 28 days away from direct heat and light, as long as the temperature is not greater than 86°F (30°C).

Open (In-Use) SoloStar disposable insulin device:

The opened (in-use) SoloStar should NOT be refrigerated but should be kept at room temperature (below 86°F [30°C]) away from direct heat and light. The opened (in-use) SoloStar device must be discarded 28 days after being opened.

These storage conditions are summarized in the following table:

 | Not in-use (unopened) Refrigerated | Not in-use (unopened) Room Temperature | In-use (opened) (See Temperature Below)
10 mL Vial | Until expiration date | 28 days | 28 days Refrigerated or room temperature
3 mL SoloStar disposable insulin device® | Until expiration date | 28 days | 28 days Room temperature only (Do not refrigerate)

16.3 Preparation and handling

Parenteral drug products should be inspected visually prior to administration whenever the solution and the container permit. LANTUS must only be used if the solution is clear and colorless with no particles visible.

Mixing and diluting: LANTUS must NOT be diluted or mixed with any other insulin or solution [S . ee ] Warnings and Precautions (5.2)

The syringes must not contain any other medicinal product or residue. Vial:

: If SoloStar disposable insulin device, malfunctions, LANTUS may be drawn from the cartridge system or from SoloStar into a U-100 syringe and injected. SoloStar

17. PATIENT COUNSELING INFORMATION

17.1 Instructions for patients

Patients should be informed that changes to insulin regimens must be made cautiously and only under medical supervision.

Patients should be informed about the potential side effects of insulin therapy, including lipodystrophy (and the need to rotate injection sites within the same body region), weight gain, allergic reactions, and hypoglycemia. Patients should be informed that the ability to concentrate and react may be impaired as a result of hypoglycemia. This may present a risk in situations where these abilities are especially important, such as driving or operating other machinery. Patients who have frequent hypoglycemia or reduced or absent warning signs of hypoglycemia should be advised to use caution when driving or operating machinery.

Accidental mix-ups between LANTUS and other insulins, particularly short-acting insulins, have been reported. To avoid medication errors between LANTUS and other insulins, patients should be instructed to always check the insulin label before each injection.

LANTUS must only be used if the solution is clear and colorless with no particles visible Patients must be advised that LANTUS must NOT be diluted or mixed with any other insulin or solution ..

Patients should be advised not to share disposable or reusable insulin devices or needles with other patients, because doing so carries a risk for transmission of blood-borne pathogens.

Patients should be instructed on self-management procedures including glucose monitoring, proper injection technique, and management of hypoglycemia and hyperglycemia. Patients must be instructed on handling of special situations such as intercurrent conditions (illness, stress, or emotional disturbances), an inadequate or skipped insulin dose, inadvertent administration of an increased insulin dose, inadequate food intake, and skipped meals.

Patients with diabetes should be advised to inform their health care professional if they are pregnant or are contemplating pregnancy.

Refer patients to the LANTUS "Patient Information" for additional information.

17.2 FDA approved patient labeling

See attached document at end of Full Prescribing Information.

sanofi-aventis U.S. LLC

Bridgewater, NJ 08807

A SANOFI COMPANY

©2013 sanofi-aventis U.S. LLC

PATIENT INFORMATION

Patient Information LANTUS 10 mL vial (1000 units per vial) 100 units per mL (U-100) (insulin glargine [recombinant DNA origin] injection)
®

- What is the most important information I should know about LANTUS?
- What is LANTUS?
- Who should NOT take LANTUS?
- How should I use LANTUS?
- What kind of syringe should I use?
- Mixing with LANTUS
- Instructions for Use
  - How do I draw the insulin into the syringe?
  - How do I inject LANTUS?
- What can affect how much insulin I need?
- What are the possible side effects of LANTUS and other insulins?
- How should I store LANTUS?
- General Information about LANTUS

Read this "Patient Information" that comes with LANTUS (LAN-tus) before you start using it and each time you get a refill because there may be new information. This leaflet does not take the place of talking with your healthcare provider about your condition or treatment. If you have questions about LANTUS or about diabetes, talk with your healthcare provider.

What is the most important information I should know about LANTUS?

- Any change of insulin should be made cautiously and only under medical supervision. Changes in insulin strength, manufacturer, type (for example: Regular, NPH, analogs), species (beef, pork, beef-pork, human) or method of manufacture (recombinant DNA versus animal source insulin) may need a change in the dose. This dose change may be needed right away or later on during the first several weeks or months on the new insulin. Doses of oral anti-diabetic medicines may also need to change, if your insulin is changed. Do not change the insulin you are using without talking to your healthcare provider.
- Your healthcare provider will tell you how often you should test your blood sugar level, and what to do if it is high or low. You must test your blood sugar levels while using an insulin, such as LANTUS.
- It will not work and you may lose blood sugar control, which could be serious. Do NOT dilute or mix LANTUS with any other insulin or solution.
- comes as U-100 insulin and contains 100 units of LANTUS per milliliter (mL). One milliliter of U-100 insulin contains 100 units of insulin. (1 mL = 1 cc). LANTUS

What is Diabetes?

- Your body needs insulin to turn sugar (glucose) into energy. If your body does not make enough insulin, you need to take more insulin so you will not have too much sugar in your blood.
- Insulin injections are important in keeping your diabetes under control. But the way you live, your diet, careful checking of your blood sugar levels, exercise, and planned physical activity, all work with your insulin to help you control your diabetes.

What is LANTUS?

- LANTUS (insulin glargine [recombinant DNA origin]) is a long-acting insulin. Because LANTUS is made by recombinant DNA technology (rDNA) and is chemically different from the insulin made by the human body, it is called an insulin analog. LANTUS is used to treat patients with diabetes for the control of high blood sugar. It is used once a day to lower blood sugar.
- LANTUS is a clear, colorless, sterile solution for injection under the skin (subcutaneously).
- The active ingredient in LANTUS is insulin glargine. The concentration of insulin glargine is 100 units per milliliter (mL), or U-100. LANTUS also contains zinc, metacresol, glycerol, polysorbate 20 and water for injection as inactive ingredients. Hydrochloric acid and/or sodium hydroxide may be added to adjust the pH.
- You need a prescription to get LANTUS. Always be sure you receive the right insulin from the pharmacy.

Who should NOT take LANTUS?

or any of the inactive ingredients in LANTUS. Check with your healthcare provider if you are not sure. Do not take LANTUS if you are allergic to insulin glargine

Before starting LANTUS, tell your healthcare provider about all your medical conditions including if you:

- Your dose may need to be adjusted. have liver or kidney problems.
- It is not known if LANTUS may harm your unborn baby. It is very important to maintain control of your blood sugar levels during pregnancy. Your healthcare provider will decide which insulin is best for you during your pregnancy. are pregnant or plan to become pregnant.
- It is not known whether LANTUS passes into your milk. Many medicines, including insulin, pass into human milk, and could affect your baby. Talk to your healthcare provider about the best way to feed your baby. are breast-feeding or plan to breast-feed.
- prescription and non-prescription medicines, vitamins, and herbal supplements. about all the medicines you take including
- , especially ones commonly called TZDs (thiazolidinediones). if you take any other medicines
- . If you have heart failure, it may get worse while you take TZDs with Lantus. if you have heart failure or other heart problems

How should I use LANTUS?

See the including the "Instructions for Use""How do I draw the insulin into the syringe?" section for additional information.

- Follow the instructions given by your healthcare provider about the type or types of insulin you are using. Do not make any changes with your insulin unless you have talked to your healthcare provider. Your insulin needs may change because of illness, stress, other medicines, or changes in diet or activity level. Talk to your healthcare provider about how to adjust your insulin dose.
- You may take LANTUS at any time during the day but you must take it at the same time every day.
- Only use LANTUS that is clear and colorless. If your LANTUS is cloudy or slightly colored, return it to your pharmacy for a replacement.
- Follow your healthcare provider's instructions for testing your blood sugar.
- Inject LANTUS under your skin (subcutaneously) in your upper arm, abdomen (stomach area), or thigh (upper leg). Never inject it into a vein or muscle.
- Change (rotate) injection sites within the same body area.

What kind of syringe should I use?

- Always use a syringe that is marked for U-100 insulin. If you use other than U-100 insulin syringe, you may get the wrong dose of insulin causing serious problems for you, such as a blood sugar level that is too low or too high. Always use a new needle and syringe each time you give LANTUS injection.
- NEEDLES AND SYRINGES MUST NOT BE SHARED.
- Disposable syringes and needles should be used only once. Used syringe and needle should be placed in sharps containers (such as red biohazard containers), hard plastic containers (such as detergent bottles), or metal containers (such as an empty coffee can). Such containers should be sealed and disposed of properly.

Mixing with LANTUS

- It will not work as intended and you may lose blood sugar control, which could be serious. Do NOT dilute or mix LANTUS with any other insulin or solution.

Instructions for Use

How do I draw the insulin into the syringe?

- The syringe must be new and does not contain any other medicine.
- Do not mix LANTUS with any other type of insulin.

Follow these steps:

1. Wash your hands with soap and water or with alcohol.
2. Check the insulin to make sure it is clear and colorless. Do not use the insulin after the expiration date stamped on the label, if it is colored or cloudy, or if you see particles in the solution.
3. If you are using a new vial, remove the protective cap. remove the stopper. Do not
4. Wipe the top of the vial with an alcohol swab. You do not have to shake the vial of LANTUS before use.
5. Use a new needle and syringe every time you give an injection. Use disposable syringes and needles only once. Throw them away properly. share needles and syringes. Never
6. Draw air into the syringe equal to your insulin dose. Put the needle through the rubber top of the vial and push the plunger to inject the air into the vial.
7. Leave the syringe in the vial and turn both upside down. Hold the syringe and vial firmly in one hand.
8. Make sure the tip of the needle is in the insulin. With your free hand, pull the plunger to withdraw the correct dose into the syringe.
9. Before you take the needle out of the vial, check the syringe for air bubbles. If bubbles are in the syringe, hold the syringe straight up and tap the side of the syringe until the bubbles float to the top. Push the bubbles out with the plunger and draw insulin back in until you have the correct dose.
10. Remove the needle from the vial. Do not let the needle touch anything. You are now ready to inject.

How do I inject LANTUS?

Inject LANTUS under your skin. Take LANTUS as prescribed by your healthcare provider.

Follow these steps:

1. Decide on an injection area - either upper arm, thigh or abdomen. Injection sites within an injection area must be different from one injection to the next.
2. Use alcohol or soap and water to clean the injection site. The injection site should be dry before you inject.
3. Pinch the skin. Stick the needle in the way your healthcare provider showed you. Release the skin.
4. Slowly push in the plunger of the syringe all the way, making sure you have injected all the insulin. Leave the needle in the skin for about 10 seconds.
5. Pull the needle straight out and gently press on the spot where you injected yourself for several seconds. Do not rub the area.
6. Follow your healthcare provider's instructions for throwing away the used needle and syringe. Do not recap the used needle. Used needle and syringe should be placed in sharps containers (such as red biohazard containers), hard plastic containers (such as detergent bottles), or metal containers (such as an empty coffee can). Such containers should be sealed and disposed of properly.

What can affect how much insulin I need?

Illness may change how much insulin you need. It is a good idea to think ahead and make a "sick day" plan with your healthcare provider in advance so you will be ready when this happens. Be sure to test your blood sugar more often and call your healthcare provider if you are sick. Illness.

Other medicines, including prescription and non-prescription medicines, vitamins, and herbal supplements, can change the way insulin works. You may need a different dose of insulin when you are taking certain other medicines. including prescription and non-prescription medicines, vitamins, and herbal supplements. You may want to keep a list of the medicines you take. You can show this list to your healthcare provider anytime you get a new medicine or refill. Your healthcare provider will tell you if your insulin dose needs to be changed. Medicines. Many medicines can affect your insulin needs. Know all the medicines you take,

The amount of food you eat can affect your insulin needs. If you eat less food, skip meals, or eat more food than usual, you may need a different dose of insulin. Talk to your healthcare provider if you change your diet so that you know how to adjust your LANTUS and other insulin doses. Meals.

Alcohol, including beer and wine, may affect the way LANTUS works and affect your blood sugar levels. Talk to your healthcare provider about drinking alcohol. Alcohol.

Exercise or activity level may change the way your body uses insulin. Check with your healthcare provider before you start an exercise program because your dose may need to be changed. Exercise or Activity level.

If you travel across time zones, talk with your healthcare provider about how to time your injections. When you travel, wear your medical alert identification. Take extra insulin and supplies with you. Travel.

The effects of LANTUS on an unborn child or on a nursing baby are unknown. Therefore, tell your healthcare provider if you are planning to have a baby, are pregnant, or nursing a baby. Good control of diabetes is especially important during pregnancy and nursing. Pregnancy or nursing.

What are the possible side effects of LANTUS and other insulins?

Insulins, including LANTUS, can cause hypoglycemia (low blood sugar), hyperglycemia (high blood sugar), allergy, and skin reactions.

Hypoglycemia (low blood sugar):

Hypoglycemia is often called an "insulin reaction" or "low blood sugar". It may happen when you do not have enough sugar in your blood. Common causes of hypoglycemia are illness, emotional or physical stress, too much insulin, too little food or missed meals, and too much exercise or activity.

Early warning signs of hypoglycemia may be different, less noticeable or not noticeable at all in some people. That is why it is important to check your blood sugar as you have been advised by your healthcare provider.

: Hypoglycemia can happen with

- This can happen when too much insulin is injected. Taking too much insulin.
- . This can happen if a meal or snack is missed or delayed. Not enough carbohydrate (sugar or starch) intake
- that decreases the amount of sugar absorbed by your body. Vomiting or diarrhea
- Intake of alcohol.
- Be sure to discuss all your medicines with your healthcare provider. Medicines that affect insulin. Do not start any new medicines until you know how they may affect your insulin dose.
- These conditions include diseases of the adrenal glands, the pituitary, the thyroid gland, the liver, and the kidney. Medical conditions that can affect your blood sugar levels or insulin.
- This can happen if you exercise too much or have a fever. Too much glucose use by the body.
- Injecting insulin the wrong way or in the wrong injection area.

Hypoglycemia can be mild to severe. Its onset may be rapid. Some patients have few or no warning symptoms, including:

- patients with diabetes for a long time
- patients with diabetic neuropathy (nerve problems)
- or patients using certain medicines for high blood pressure or heart problems.

Hypoglycemia may reduce your ability to drive a car or use mechanical equipment and you may risk injury to yourself or others.

Severe hypoglycemia can be dangerous and can cause temporary or permanent harm to your heart or brain. It may cause unconsciousness, seizures, or death.

Symptoms of hypoglycemia may include:

- anxiety, irritability, restlessness, trouble concentrating, personality changes, mood changes, or other abnormal behavior
- tingling in your hands, feet, lips, or tongue
- dizziness, light-headedness, or drowsiness
- nightmares or trouble sleeping
- headache
- blurred vision
- slurred speech
- palpitations (fast heart beat)
- sweating
- tremor (shaking)
- unsteady gait (walking).

If you have hypoglycemia often or it is hard for you to know if you have the symptoms of hypoglycemia, talk to your healthcare provider.

Mild to moderate hypoglycemia is treated by eating or drinking carbohydrates, such as fruit juice, raisins, sugar candies, milk or glucose tablets. Talk to your healthcare provider about the amount of carbohydrates you should eat to treat mild to moderate hypoglycemia.

Severe hypoglycemia may require the help of another person or emergency medical people. A person with hypoglycemia who is unable to take foods or liquids with sugar by mouth, or is unconscious needs medical help fast and will need treatment with a glucagon injection or glucose given intravenously (IV). Without medical help right away, serious reactions or even death could happen.

Hyperglycemia (high blood sugar):

Hyperglycemia happens when you have too much sugar in your blood. Usually, it means there is not enough insulin to break down the food you eat into energy your body can use. Hyperglycemia can be caused by a fever, an infection, stress, eating more than you should, taking less insulin than prescribed, or it can mean your diabetes is getting worse.

Hyperglycemia can happen with:

- . This can happen from: Insufficient (too little) insulin
  - injecting too little or no insulin
  - incorrect storage (freezing, excessive heat)
  - use after the expiration date.
- . This can happen if you eat larger meals, eat more often, or increase the amount of carbohydrate in your meals. Too much carbohydrate intake
- Be sure to discuss all your medicines with your healthcare provider. Medicines that affect insulin. Do not start any new medicines until you know how they may affect your insulin dose.
- . These medical conditions include fevers, infections, heart attacks, and stress. Medical conditions that affect insulin
- Injecting insulin the wrong way or in the wrong injection area.

Testing your blood or urine often will let you know if you have hyperglycemia. If your tests are often high, tell your healthcare provider so your dose of insulin can be changed.

Hyperglycemia can be mild or severe. Hyperglycemia can progress to diabetic ketoacidosis (DKA) or very high glucose levels (hyperosmolar coma) and result in unconsciousness and death.

Although diabetic ketoacidosis occurs most often in patients with type 1 diabetes, it can also happen in patients with type 2 diabetes who become very sick. Because some patients get few symptoms of hyperglycemia, it is important to check your blood sugar/urine sugar and ketones regularly.

Symptoms of hyperglycemia include:

- confusion or drowsiness
- increased thirst
- decreased appetite, nausea, or vomiting
- rapid heart rate
- increased urination and dehydration (too little fluid in your body).

Symptoms of DKA also include:

- fruity smelling breath
- fast, deep breathing
- stomach area (abdominal) pain.

Severe or continuing hyperglycemia or DKA needs evaluation and treatment right away by your healthcare provider.

Do not use LANTUS to treat diabetic ketoacidosis.

Other possible side effects of LANTUS include:

Serious allergic reactions:

Some times severe, life-threatening allergic reactions can happen with insulin. If you think you are having a severe allergic reaction, get medical help right away. Signs of insulin allergy include:

- rash all over your body
- shortness of breath
- wheezing (trouble breathing)
- fast pulse
- sweating
- low blood pressure.

Reactions at the injection site:

Injecting insulin can cause the following reactions on the skin at the injection site:

- little depression in the skin (lipoatrophy)
- skin thickening (lipohypertrophy)
- red, swelling, itchy skin (injection site reaction).

You can reduce the chance of getting an injection site reaction if you change (rotate) the injection site each time. An injection site reaction should clear up in a few days or a few weeks. If injection site reactions do not go away or keep happening, call your healthcare provider.

Swelling of your hands and feet (edema)

Weight gain

Taking certain diabetes pills called thiazolidinediones or "TZDs" with Lantus may cause heart failure in some people. This can happen even if you have never had heart failure or heart problems before. If you already have heart failure it may get worse while you take TZDs with Lantus. Your healthcare provider should monitor you closely while you are taking TZDs with Lantus. Tell your healthcare provider if you have any new or worse symptoms of heart failure including: Heart Failure.

- shortness of breath
- swelling of your ankles or feet
- sudden weight gain

During treatment with TZDs and Lantus, the TZD dose may need to be adjusted or stopped by your healthcare provider if you have new or worse heart failure.

Tell your healthcare provider if you have any side effects that bother you.

These are not all the side effects of LANTUS. Ask your healthcare provider or pharmacist for more information.

How should I store LANTUS?

- Unopened vial:
  Store new (unopened) LANTUS vials in a refrigerator (not the freezer) between 36°F to 46°F (2°C to 8°C). Do not freeze LANTUS. Keep LANTUS out of direct heat and light. If a vial has been frozen or overheated, throw it away.
- : Open (In-Use) vial
  Once a vial is opened, you can keep it in a refrigerator or at room temperature (below 86°F [30°C]) but away from direct heat and light. Opened vial, either kept in a refrigerator or at room temperature, should be discarded 28 days after the first use even if it still contains LANTUS. Do not leave your insulin in a car on a summer day.
  These storage conditions are summarized in the following table:
   | Not in-use (unopened) | Not in-use (unopened) | In-use (opened)
   | Refrigerated | Room Temperature | (See Temperature Below)
  10 mL Vial | Until expiration date | 28 days | 28 days Refrigerated or room temperature
- Do not use a vial of LANTUS after the expiration date stamped on the label.
- Do not use LANTUS if it is cloudy, colored, or if you see particles.

General Information about LANTUS

- Use LANTUS only to treat your diabetes. give or share LANTUS with another person, even if they have diabetes also. It may harm them. Do not
- This leaflet summarizes the most important information about LANTUS. If you would like more information, talk with your healthcare provider. You can ask your doctor or pharmacist for information about LANTUS that is written for healthcare professionals. For more information about LANTUS call 1-800-633-1610 or go to website www.lantus.com.

ADDITIONAL INFORMATION

is a national magazine designed especially for patients with diabetes and their families and is available by subscription from the American Diabetes Association (ADA), P.O.Box 363, Mt. Morris, IL 61054-0363, 1-800-DIABETES (1-800-342-2383). You may also visit the ADA website at www.diabetes.org. DIABETES FORECAST

Another publication, , is available from the Juvenile Diabetes Research Foundation International (JDRF), 120 Wall Street, 19th Floor, New York, New York 10005, 1-800-JDF-CURE (1-800-533-2873). You may also visit the JDRF website at www.jdf.org. COUNTDOWN

To get more information about diabetes, check with your healthcare professional or diabetes educator or visit www.DiabetesWatch.com.

Additional information about LANTUS can be obtained by calling 1-800-633-1610 or by visiting www.lantus.com.

Rev. October 2013

sanofi-aventis U.S. LLC Bridgewater, NJ 08807 A SANOFI COMPANY

©2013 sanofi-aventis U.S. LLC

Patient Information LANTUS SOLOSTAR 3 mL disposable insulin delivery device (300 units per device) 100 units per mL (U-100) (insulin glargine [recombinant DNA origin] injection)
®®

- What is the most important information I should know about LANTUS?
- What is LANTUS?
- Who should NOT take LANTUS?
- How should I use LANTUS?
- Mixing with LANTUS
- Instructions for Use
- What can affect how much insulin I need?
- What are the possible side effects of LANTUS and other insulins?
- How should I store LANTUS?
- General Information about LANTUS

Read this "Patient Information" that comes with LANTUS (LAN-tus) before you start using it and each time you get a refill because there may be new information. This leaflet does not take the place of talking with your healthcare provider about your condition or treatment. If you have questions about LANTUS or about diabetes, talk with your healthcare provider.

What is the most important information I should know about LANTUS?

- Any change of insulin should be made cautiously and only under medical supervision. Changes in insulin strength, manufacturer, type (for example: Regular, NPH, analogs), species (beef, pork, beef-pork, human) or method of manufacture (recombinant DNA versus animal-source insulin) may need a change in the dose. This dose change may be needed right away or later on during the first several weeks or months on the new insulin. Doses of oral anti-diabetic medicines may also need to change, if your insulin is changed. Do not change the insulin you are using without talking to your healthcare provider.
- Your healthcare provider will tell you how often you should test your blood sugar level, and what to do if it is high or low. You must test your blood sugar levels while using an insulin, such as LANTUS.
- It will not work and you may lose blood sugar control, which could be serious. Do NOT dilute or mix LANTUS with any other insulin or solution.
- comes as U-100 insulin and contains 100 units of LANTUS per milliliter (mL). One milliliter of U-100 insulin contains 100 units of insulin. (1 mL = 1 cc). LANTUS

What is Diabetes?

- Your body needs insulin to turn sugar (glucose) into energy. If your body does not make enough insulin, you need to take more insulin so you will not have too much sugar in your blood.
- Insulin injections are important in keeping your diabetes under control. But the way you live, your diet, careful checking of your blood sugar levels, exercise, and planned physical activity, all work with your insulin to help you control your diabetes.

What is LANTUS?

- LANTUS (insulin glargine [recombinant DNA origin]) is a long-acting insulin. Because Lantus is made by recombinant DNA technology (rDNA) and is chemically different from the insulin made by the human body, it is called an insulin analog. LANTUS is used to treat patients with diabetes for the control of high blood sugar. It is used once a day to lower blood glucose.
- LANTUS is a clear, colorless, sterile solution for injection under the skin (subcutaneously).
- The active ingredient in LANTUS is insulin glargine. The concentration of insulin glargine is 100 units per milliliter (mL), or U-100. LANTUS also contains zinc, metacresol, glycerol, and water for injection as inactive ingredients. Hydrochloric acid and/or sodium hydroxide may be added to adjust the pH.
- You need a prescription to get LANTUS. Always be sure you receive the right insulin from the pharmacy.

Who should NOT take LANTUS?

or any of the inactive ingredients in LANTUS. Check with your healthcare provider if you are not sure. Do not take LANTUS if you are allergic to insulin glargine

- Before starting LANTUS, tell your healthcare provider about all your medical conditions including if you:
  - Your dose may need to be adjusted. have liver or kidney problems.
  - It is not known if LANTUS may harm your unborn baby. It is very important to maintain control of your blood sugar levels during pregnancy. Your healthcare provider will decide which insulin is best for you during your pregnancy. are pregnant or plan to become pregnant.
  - It is not known whether LANTUS passes into your milk. Many medicines, including insulin, pass into human milk, and could affect your baby. Talk to your healthcare provider about the best way to feed your baby. are breast-feeding or plan to breast-feed.
  - prescription and non-prescription medicines, vitamins and herbal supplements. are taking any other medicines including
  - , especially ones commonly called TZDs (thiazolidinediones). if you take any other medicines
  - . If you have heart failure, it may get worse while you take TZDs with Lantus. if you have heart failure or other heart problems

How should I use LANTUS?

See the " Instructions for SoloStar Use" section for additional information.

- Follow the instructions given by your healthcare provider about the type or types of insulin you are using. Do not make any changes with your insulin unless you have talked to your healthcare provider. Your insulin needs may change because of illness, stress, other medicines, or changes in diet or activity level. Talk to your healthcare provider about how to adjust your insulin dose.
- You may take LANTUS at any time during the day but you must take it at the same time every day.
- Only use LANTUS that is clear and colorless. If your LANTUS is cloudy or slightly colored, return it to your pharmacy for a replacement.
- Follow your healthcare provider's instructions for testing your blood sugar.
- Inject LANTUS under your skin (subcutaneously) in your upper arm, abdomen (stomach area), or thigh (upper leg). Never inject it into a vein or muscle.
- Change (rotate) injection sites within the same body area.
- NEEDLES AND SOLOSTAR MUST NOT BE SHARED.
- Disposable needles should be used only once. Used needle should be placed in sharps containers (such as red biohazard containers), hard plastic containers (such as detergent bottles), or metal containers (such as an empty coffee can). Such containers should be sealed and disposed of properly.

Mixing with LANTUS

- It will not work as intended and you may lose blood sugar control, which could be serious. Do NOT dilute or mix LANTUS with any other insulin or solution.

Instructions for SoloStar Use

If you have lost your leaflet or have a question, go to www.lantus.com or call 1-800-633-1610. It is important to read, understand, and follow the step-by-step instructions in the "SoloStar Instruction Leaflet" before using SoloStar disposable insulin Pen. Failure to follow the instructions may result in getting too much or too little insulin.

The following general notes should be taken into consideration before injecting Lantus:

- Always wash your hands before handling the SoloStar disposable insulin Pen.
- Always attach a new needle before use. BD Ultra-Fine™ needles are compatible with SoloStar. These are sold separately and are manufactured by BD.†
- Always perform the safety test before use.
- Check the insulin solution in the pen to make sure it is clear, colorless, and free of particles. If it is not, throw it away.
- Do NOT mix or dilute LANTUS with any other insulin or solution. LANTUS will not work if it is mixed or diluted and you may lose blood sugar control, which could be serious.
- Decide on an injection area - either upper arm, thigh, or abdomen. Do not use the same injection site as your last injection.
- After injecting LANTUS, leave the needle in the skin for an additional 10 seconds. Then pull the needle straight out. Gently press on the spot where you injected yourself for a few seconds. Do not rub the area.
- Do not drop the SoloStar disposable insulin Pen.

If your blood glucose reading is high or low, tell your healthcare provider so the dose can be adjusted.

What can affect how much insulin I need?

Illness may change how much insulin you need. It is a good idea to think ahead and make a "sick day" plan with your healthcare provider in advance so you will be ready when this happens. Be sure to test your blood sugar more often and call your healthcare provider if you are sick. Illness.

Other medicines, including prescription and non-prescription medicines, vitamins, and herbal supplements, can change the way insulin works. You may need a different dose of insulin when you are taking certain other medicines. including prescription and non-prescription medicines, vitamins and herbal supplements. You may want to keep a list of the medicines you take. You can show this list to your healthcare provider and pharmacists anytime you get a new medicine or refill. Your healthcare provider will tell you if your insulin dose needs to be changed. Medicines. Many medicines can affect your insulin needs. Know all the medicines you take,

The amount of food you eat can affect your insulin needs. If you eat less food, skip meals, or eat more food than usual, you may need a different dose of insulin. Talk to your healthcare provider if you change your diet so that you know how to adjust your LANTUS and other insulin doses. Meals.

Alcohol, including beer and wine, may affect the way LANTUS works and affect your blood sugar levels. Talk to your healthcare provider about drinking alcohol. Alcohol.

Exercise or activity level may change the way your body uses insulin. Check with your healthcare provider before you start an exercise program because your dose may need to be changed. Exercise or Activity level.

If you travel across time zones, talk with your healthcare provider about how to time your injections. When you travel, wear your medical alert identification. Take extra insulin and supplies with you. Travel.

The effects of LANTUS on an unborn child or on a nursing baby are unknown. Therefore, tell your healthcare provider if you are planning to have a baby, are pregnant, or nursing a baby. Good control of diabetes is especially important during pregnancy and nursing. Pregnancy or nursing.

What are the possible side effects of LANTUS and other insulins?

Insulins, including LANTUS, can cause hypoglycemia (low blood sugar), hyperglycemia (high blood sugar), allergy, and skin reactions.

Hypoglycemia (low blood sugar):

Hypoglycemia is often called an "insulin reaction" or "low blood sugar". It may happen when you do not have enough sugar in your blood. Common causes of hypoglycemia are illness, emotional or physical stress, too much insulin, too little food or missed meals, and too much exercise or activity.

Early warning signs of hypoglycemia may be different, less noticeable or not noticeable at all in some people. That is why it is important to check your blood sugar as you have been advised by your healthcare provider.

Hypoglycemia can happen with:

- This can happen when too much insulin is injected. Taking too much insulin.
- This can happen if a meal or snack is missed or delayed. Not enough carbohydrate (sugar or starch) intake.
- that decreases the amount of sugar absorbed by your body. Vomiting or diarrhea
- Intake of alcohol.
- Be sure to discuss all your medicines with your healthcare provider. Medicines that affect insulin. Do not start any new medicines until you know how they may affect your insulin dose.
- These conditions include diseases of the adrenal glands, the pituitary, the thyroid gland, the liver, and the kidney. Medical conditions that can affect your blood sugar levels or insulin.
- This can happen if you exercise too much or have a fever. Too much glucose use by the body.
- Injecting insulin the wrong way or in the wrong injection area.

Hypoglycemia can be mild to severe. Its onset may be rapid. Some patients have few or no warning symptoms, including:

- patients with diabetes for a long time
- patients with diabetic neuropathy (nerve problems)
- or patients using certain medicines for high blood pressure or heart problems.

Hypoglycemia may reduce your ability to drive a car or use mechanical equipment and you may risk injury to yourself or others.

Severe hypoglycemia can be dangerous and can cause temporary or permanent harm to your heart or brain. It may cause unconsciousness, seizures, or death.

Symptoms of hypoglycemia may include:

- anxiety, irritability, restlessness, trouble concentrating, personality changes, mood changes, or other abnormal behavior
- tingling in your hands, feet, lips, or tongue
- dizziness, light-headedness, or drowsiness
- nightmares or trouble sleeping
- headache
- blurred vision
- slurred speech
- palpitations (fast heart beat)
- sweating
- tremor (shaking)
- unsteady gait (walking).

If you have hypoglycemia often or it is hard for you to know if you have the symptoms of hypoglycemia, talk to your healthcare provider.

Mild to moderate hypoglycemia is treated by eating or drinking carbohydrates such as fruit juice, raisins, sugar candies, milk or glucose tablets. Talk to your healthcare provider about the amount of carbohydrates you should eat to treat mild to moderate hypoglycemia.

Severe hypoglycemia may require the help of another person or emergency medical people. A person with hypoglycemia who is unable to take foods or liquids with sugar by mouth, or is unconscious needs medical help fast and will need treatment with a glucagon injection or glucose given intravenously (IV). Without medical help right away, serious reactions or even death could happen.

Hyperglycemia (high blood sugar):

Hyperglycemia happens when you have too much sugar in your blood. Usually, it means there is not enough insulin to break down the food you eat into energy your body can use. Hyperglycemia can be caused by a fever, an infection, stress, eating more than you should, taking less insulin than prescribed, or it can mean your diabetes is getting worse.

Hyperglycemia can happen with:

- This can happen from: Insufficient (too little) insulin.
  - injecting too little or no insulin
  - incorrect storage (freezing, excessive heat)
  - use after the expiration date.
- This can happen if you eat larger meals, eat more often, or increase the amount of carbohydrate in your meals. Too much carbohydrate intake.
- Be sure to discuss all your medicines with your healthcare provider. Medicines that affect insulin. Do not start any new medicines until you know how they may affect your insulin dose.
- These medical conditions include fevers, infections, heart attacks, and stress. Medical conditions that affect insulin.
- Injecting insulin the wrong way or in the wrong injection area.

Testing your blood or urine often will let you know if you have hyperglycemia. If your tests are often high, tell your healthcare provider so your dose of insulin can be changed.

Hyperglycemia can be mild or severe. It can progress to diabetic ketoacidosis (DKA) or very high glucose levels (hyperosmolar coma) and result in unconsciousness and death.

Although diabetic ketoacidosis occurs most often in patients with type 1 diabetes,it can also happen in patients with type 2 diabetes who become very sick. Because some patients get few symptoms of hyperglycemia, it is important to check your blood sugar/urine sugar and ketones regularly.

Symptoms of hyperglycemia include:

- confusion or drowsiness
- increased thirst
- decreased appetite, nausea, or vomiting
- rapid heart rate
- increased urination and dehydration (too little fluid in your body).

Symptoms of DKA also include:

- fruity smelling breath
- fast, deep breathing
- stomach area (abdominal) pain.

Severe or continuing hyperglycemia or DKA needs evaluation and treatment right away by your healthcare provider.

Do not use LANTUS to treat diabetic ketoacidosis.

Other possible side effects of LANTUS include:

Serious allergic reactions:

Some times severe, life-threatening allergic reactions can happen with insulin. If you think you are having a severe allergic reaction, get medical help right away. Signs of insulin allergy include:

- rash all over your body
- shortness of breath
- wheezing (trouble breathing)
- fast pulse
- sweating
- low blood pressure.

Reactions at the injection site:

Injecting insulin can cause the following reactions on the skin at the injection site:

- little depression in the skin (lipoatrophy)
- skin thickening (lipohypertrophy)
- red, swelling, itchy skin (injection site reaction).

You can reduce the chance of getting an injection site reaction if you change (rotate) the injection site each time. An injection site reaction should clear up in a few days or a few weeks. If injection site reactions do not go away or keep happening call your healthcare provider.

Swelling of your hands and feet (edema)

Weight gain

Taking certain diabetes pills called thiazolidinediones or "TZDs" with Lantus may cause heart failure in some people. This can happen even if you have never had heart failure or heart problems before. If you already have heart failure it may get worse while you take TZDs with Lantus. Your healthcare provider should monitor you closely while you are taking TZDs with Lantus. Tell your healthcare provider if you have any new or worse symptoms of heart failure including: Heart Failure.

- shortness of breath
- swelling of your ankles or feet
- sudden weight gain

During treatment with TZDs and Lantus, the TZD dose may need to be adjusted or stopped by your healthcare provider if you have new or worse heart failure.

Tell your healthcare provider if you have any side effects that bother you.

These are not all the side effects of LANTUS. Ask your healthcare provider or pharmacist for more information.

How should I store LANTUS?

- Unopened SoloStar:
  Store new unopened SoloStar disposable insulin pen in a refrigerator (not the freezer) between 36°F to 46°F (2°C to 8°C). Do not freeze LANTUS. Keep LANTUS out of direct heat and light. If a disposable insulin pen has been frozen or overheated, throw it away.
- Open (In-Use) SoloStar:
  Once SoloStar is opened (in-use), SoloStar should be refrigerated but should be kept at room temperature (below 86°F [30°C]) away from direct heat and light. The opened (in-use) SoloStar kept at room temperature must be discarded after 28 days. NOT

These storage conditions are summarized in the following table:

 | Not in-use (unopened) Refrigerated | Not in-use (unopened) Room Temperature | In-use (opened) Room Temperature (Do not refrigerate)
3 mL SoloStar disposable insulin device | Until expiration date | 28 days | 28 days

- Do not use SoloStar with LANTUS after the expiration date stamped on the label.
- Do not use LANTUS if it is cloudy, colored, or if you see particles.

General Information about LANTUS

- Use LANTUS only to treat your diabetes. give or share LANTUS with another person, even if they have diabetes also. It may harm them. Do not
- This leaflet summarizes the most important information about LANTUS. If you would like more information, talk with your healthcare provider. You can ask your healthcare provider or pharmacist for information about LANTUS that is written for healthcare professionals. For more information about LANTUS call 1-800-633-1610 or go to website www.lantus.com.

ADDITIONAL INFORMATION

is a national magazine designed especially for patients with diabetes and their families and is available by subscription from the American Diabetes Association (ADA), P.O. Box 363, Mt. Morris, IL 61054-0363, 1-800-DIABETES (1-800-342-2383). You may also visit the ADA website at www.diabetes.org. DIABETES FORECAST

Another publication, , is available from the Juvenile Diabetes Research Foundation International (JDRF), 120 Wall Street, 19th Floor, New York, New York 10005, 1-800-JDF-CURE (1-800-533-2873). You may also visit the JDRF website at www.jdf.org. COUNTDOWN

To get more information about diabetes, check with your healthcare professional or diabetes educator or visit www.DiabetesWatch.com.

Additional information about LANTUS can be obtained by calling 1-800-633-1610 or by visiting www.lantus.com.

Rev. December 2013

sanofi-aventis U.S. LLC Bridgewater, NJ 08807 A SANOFI COMPANY

©2013 sanofi-aventis U.S. LLC

Lantus and SoloStar are a registered trademark of sanofi-aventis U.S. LLC The brands listed are the trademarks of their respective owners and are not trademarks of sanofi-aventis U.S. LLC®®
†

LANTUS SOLOSTAR (insulin glargine [rDNA origin] injection)®®

Instruction Leaflet

Your healthcare professional has decided that SoloStar is right for you. Talk with your healthcare professional about proper injection technique before using SoloStar.®

Read these instructions carefully before using your SoloStar. If you are not able to follow all the instructions completely on your own, use SoloStar only if you have help from a person who is able to follow the instructions.

Follow these instructions completely each time you use SoloStar to ensure that you get an accurate dose. If you do not follow these instructions you may get too much or too little insulin, which may affect your blood glucose.

SoloStar is a disposable pen for the injection of insulin. Each SoloStar contains in total 300 units of insulin. You can set doses from 1 to 80 units in steps of 1 unit. The pen plunger moves with each dose. The plunger will only move to the end of the cartridge when 300 units of insulin have been given.

Keep this leaflet for future reference.

If you have any questions about SoloStar or about diabetes, ask your healthcare professional, go to www.lantus.com or call sanofi-aventis at 1-800-633-1610.

Important information for use of SoloStar:

- Always attach a new needle before each use.
  BD Ultra-Fine needles are compatible with SoloStar. These are sold separately and are manufactured by BD. Contact your healthcare professional for further information.® [The brands listed are the registered trademarks of their respective owners and are not trademarks of sanofi-aventis U.S. LLC]
- Always perform the safety test before each injection.
- Do not select a dose or press the injection button without a needle attached.
- This pen is only for your use. Do not share it with anyone else.
- If your injection is given by another person, special caution must be taken by this person to avoid accidental needle injury and transmission of infection.
- Never use SoloStar if it is damaged or if you are not sure that it is working properly.
- Always have a spare SoloStar in case your SoloStar is lost or damaged.

Step 1. Check the insulin

A. Check the label on your SoloStar to make sure you have the correct insulin. The Lantus SoloStar is grey with a purple injection button. ®®
B. Take off the pen cap.
C. Check the appearance of your insulin. Lantus is a clear insulin. Do not use this SoloStar if the insulin is cloudy, colored or has particles.

Step 2. Attach the needle

Always use a new sterile needle for each injection. This helps prevent contamination, and potential needle blocks.

A. Wipe the Rubber Seal with alcohol.

B. Remove the protective seal from a new needle.
C. Line up the needle with the pen, and keep it straight as you attach it (screw or push on, depending on the needle type).

- If the needle is not kept straight while you attach it, it can damage the rubber seal and cause leakage, or break the needle.

Step 3. Perform a Safety test

Performing the safety test ensures that you get an accurate dose by: perform the safety test before each injection. Always

- ensuring that pen and needle work properly
- removing air bubbles

A. Select a dose of 2 units by turning the dosage selector.
B. Take off the outer needle cap and keep it to remove the used needle after injection. Take off the inner needle cap and discard it.
C. Hold the pen with the needle pointing upwards.
D. Tap the insulin reservoir so that any air bubbles rise up towards the needle.
E. Press the injection button all the way in. Check if insulin comes out of the needle tip.

You may have to perform the safety test several times before insulin is seen.

- If no insulin comes out, check for air bubbles and repeat the safety test two more times to remove them.
- If still no insulin comes out, the needle may be blocked. Change the needle and try again.
- If no insulin comes out after changing the needle, your SoloStar may be damaged. Do not use this SoloStar.

Step 4. Select the dose

You can set the dose in steps of 1 unit, from a minimum of 1 unit to a maximum of 80 units. If you need a dose greater than 80 units, you should give it as two or more injections.

A. Check that the dose window shows "0" following the safety test.
B. Select your required dose (in the below, the selected dose is 30 units). If you turn past your dose, you can turn back down. example

- Do not push the injection button while turning, as insulin will come out.
- You cannot turn the dosage selector past the number of units left in the pen. Do not force the dosage selector to turn. In this case, either you can inject what is remaining in the pen and complete your dose with a new SoloStar or use a new SoloStar for your full dose.

Step 5. Inject the dose

A. Use the injection method as instructed by your healthcare professional.
B. Insert the needle into the skin.
C. Deliver the dose by pressing the injection button in all the way. The number in the dose window will return to "0" as you inject.
D. Keep the injection button pressed all the way in. This ensures that the full dose will be delivered. Slowly count to 10 before you withdraw the needle from the skin.

Step 6. Remove and discard the needle

Always remove the needle after each injection and store SoloStar without a needle attached. This helps prevent:

- Contamination and/or infection
- Entry of air into the insulin reservoir and leakage of insulin, which can cause inaccurate dosing.

A. Put the outer needle cap back on the needle, and use it to unscrew the needle from the pen. To reduce the risk of accidental needle injury, never replace the inner needle cap.
  - If your injection is given by another person, special caution must be taken by this person when removing and disposing the needle. Follow recommended safety measures for removal and disposal of needles (e.g. a one handed capping technique) in order to reduce the risk of accidental needle injury and transmission of infectious diseases.
B. Dispose of the needle safely. Used needles should be placed in sharps containers (such as red biohazard containers), hard plastic containers (such as detergent bottles), or metal containers (such as an empty coffee can). Such containers should be sealed and disposed of properly. If you are giving an injection to a third person, you should remove the needle in an approved manner to avoid needle-stick injuries.
C. Always put the pen cap back on the pen, then store the pen until your next injection.

Storage Instructions

Please check the leaflet for the insulin for complete instructions on how to store SoloStar.

If your SoloStar is in cool storage, take it out 1 to 2 hours before you inject to allow it to warm up. Cold insulin is more painful to inject.

Keep SoloStar out of the reach and sight of children.

Keep your SoloStar in cool storage (36°F - 46°F [2°C – 8°C]) until first use. Do not allow it to freeze. Do not put it next to the freezer compartment of your refrigerator, or next to a freezer pack.

Once you take your SoloStar out of cool storage, for use or as a spare, you can use it for up to 28 days. During this time it can be safely kept at room temperature up to 86°F (30°C). Do not use it after this time.

Do not use SoloStar after the expiration date printed on the label of the pen or on the carton.

Protect SoloStar from light.

Discard your used SoloStar as required by your local authorities.

Maintenance

Protect your SoloStar from dust and dirt.

You can clean the outside of your SoloStar by wiping it with a damp cloth.

Do not soak, wash or lubricate the pen as this may damage it.

Your SoloStar is designed to work accurately and safely. It should be handled with care. Avoid situations where SoloStar might be damaged. If you are concerned that your SoloStar may be damaged, use a new one.

SoloStar in use must not be stored in a refrigerator.

sanofi-aventis U.S. LLC Bridgewater, NJ 08807 A SANOFI COMPANY

November 2013 Date of revision:

©2013 sanofi-aventis U.S. LLC